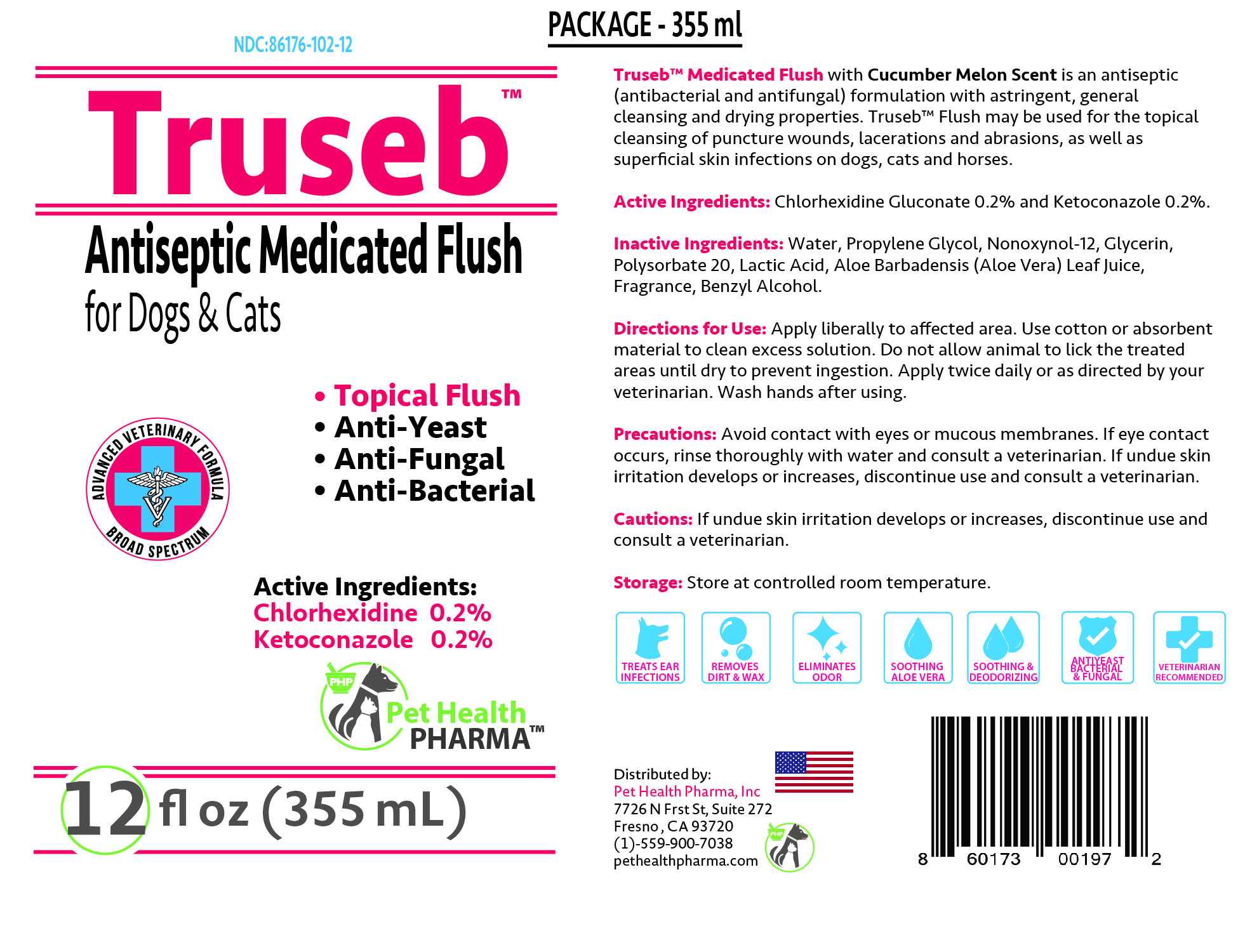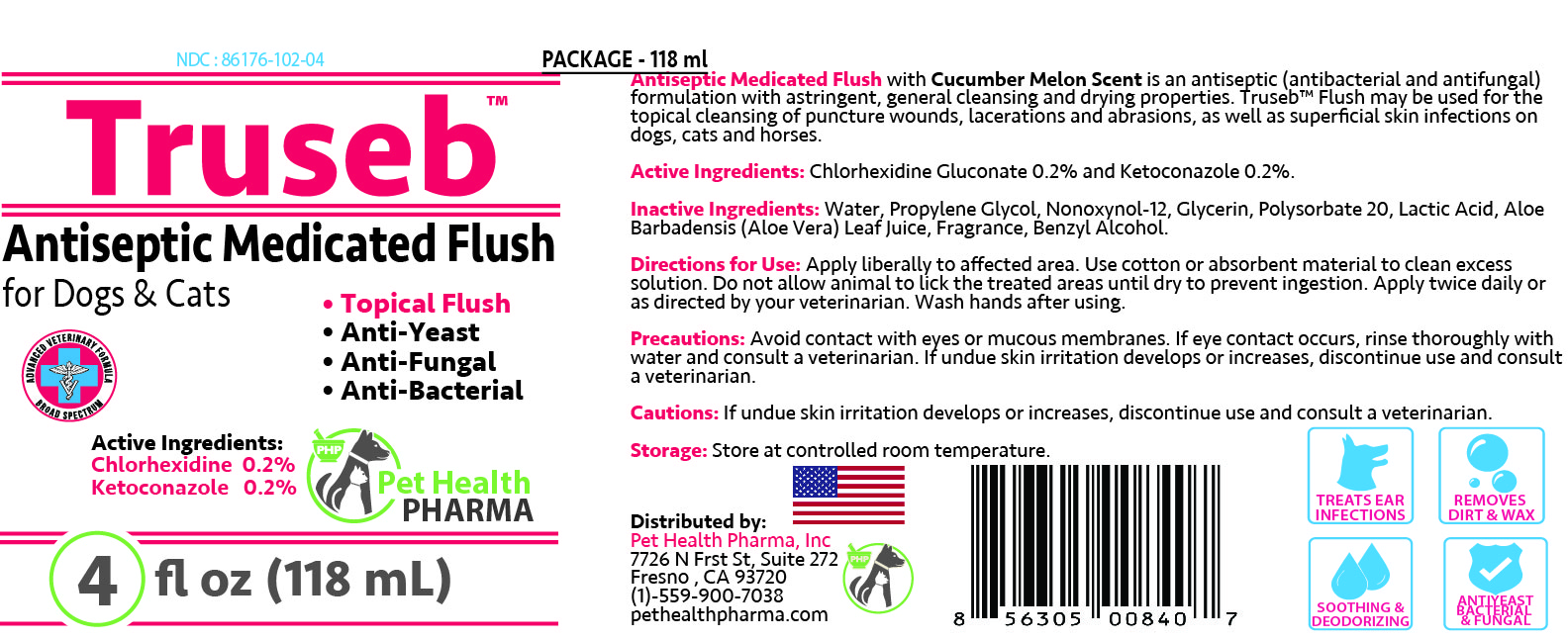 DRUG LABEL: TRUSEB ANTISEPTIC ANTI-BACTERIAL AND ANTI-FUNGAL MEDICATED FLUSH FOR DOGS AND CATS
NDC: 86176-102 | Form: SOLUTION
Manufacturer: Pet Health Pharma, LLC
Category: animal | Type: OTC ANIMAL DRUG LABEL
Date: 20210202

ACTIVE INGREDIENTS: CHLORHEXIDINE GLUCONATE 2 mg/1 mL; KETOCONAZOLE 1 mg/1 mL
INACTIVE INGREDIENTS: WATER; PROPYLENE GLYCOL; NONOXYNOL-12; GLYCERIN; POLYSORBATE 20; LACTIC ACID, UNSPECIFIED FORM; BENZYL ALCOHOL; ALOE VERA LEAF

TRUSEB ANTISEPTIC ANTI-BACTERIAL AND ANTI-FUNGAL MEDICATED FLUSH FOR DOGS AND CATS

ACTIVE INGREDIENTS:

Chlorhexidine Gluconate 0.2% and Ketoconazole 0.2%

PURPOSE:

Anti-Bacterial & Anti-Fungal

INACTIVE INGREDIENT:

Water, Propylene Glycol, Nonoxynol-12, Glycerin, Polysorbate 20, Lactic Acid, Aloe Barbadensis (Aloe Vera) Leaf Juice, Fragrance, Benzyl Alcohol.

INDICATIONS & USAGE:

Truseb™ Medicated Flush with Cucumber Melon Scent is an antiseptic (Anti-Bacterial and Anti-Fungal) formulation with astringent, general cleansing and drying properties containing Chlorhexidine Gluconate, Ketoconazole, and soothing Aloe Vera Leaf Juice. Truseb™ Flush may be used for the topical cleansing of puncture wounds, lacerations and abrasions, as well as superficial skin infections on dogs, cats and horses.

DOSAGE & ADMINISTRATION:

Apply liberally to affected area. Use cotton or absorbent material to clean excess solution. Do not allow animal to lick the treated areas until dry to prevent ingestion. Apply twice daily or as directed by your veterinarian. Wash hands after using.

PRECAUTIONS:

Avoid contact with eyes or mucous membranes. If undue skin irritation develops or increases, discontinue use and consult your veterinarian. For animal use only. For topical use only. In case of contact, flush eyes with water and seek medical attention if undue irritation persists. Keep out of the reach of children.

STORAGE AND HANDLING:

Store at controlled room temperature.

SPL UNCLASSIFIED SECTION:

MADE IN USA

Antiseptic Medicated Flush

for Dogs & Cats

- Topical Flush
- Anti-Yeast
- Anti-Fungal
- Anti-Bacterial

ADVANCED VETERINARY FORMULA

BROAD SPECTRUM

TREATS EAR INFECTIONS

REMOVES DIRT & WAX

ELIMINATES ORDER

SOOTHING ALOE VERA

SOOTHING & DEODORIZING

ANTIYEAST BACTERIAL & FUNGAL

VETERINARIAN RECOMMENDED

Cucumber Melon Scent
Distributed by:
Pet Health Pharma, Inc
7726 N Frst St, Suite 272
Fresno , CA 93720
(1)-559-900-7038
pethealthpharma.com

INDICATIONS & USAGE:

Add image transcription here...

Add image transcription here...